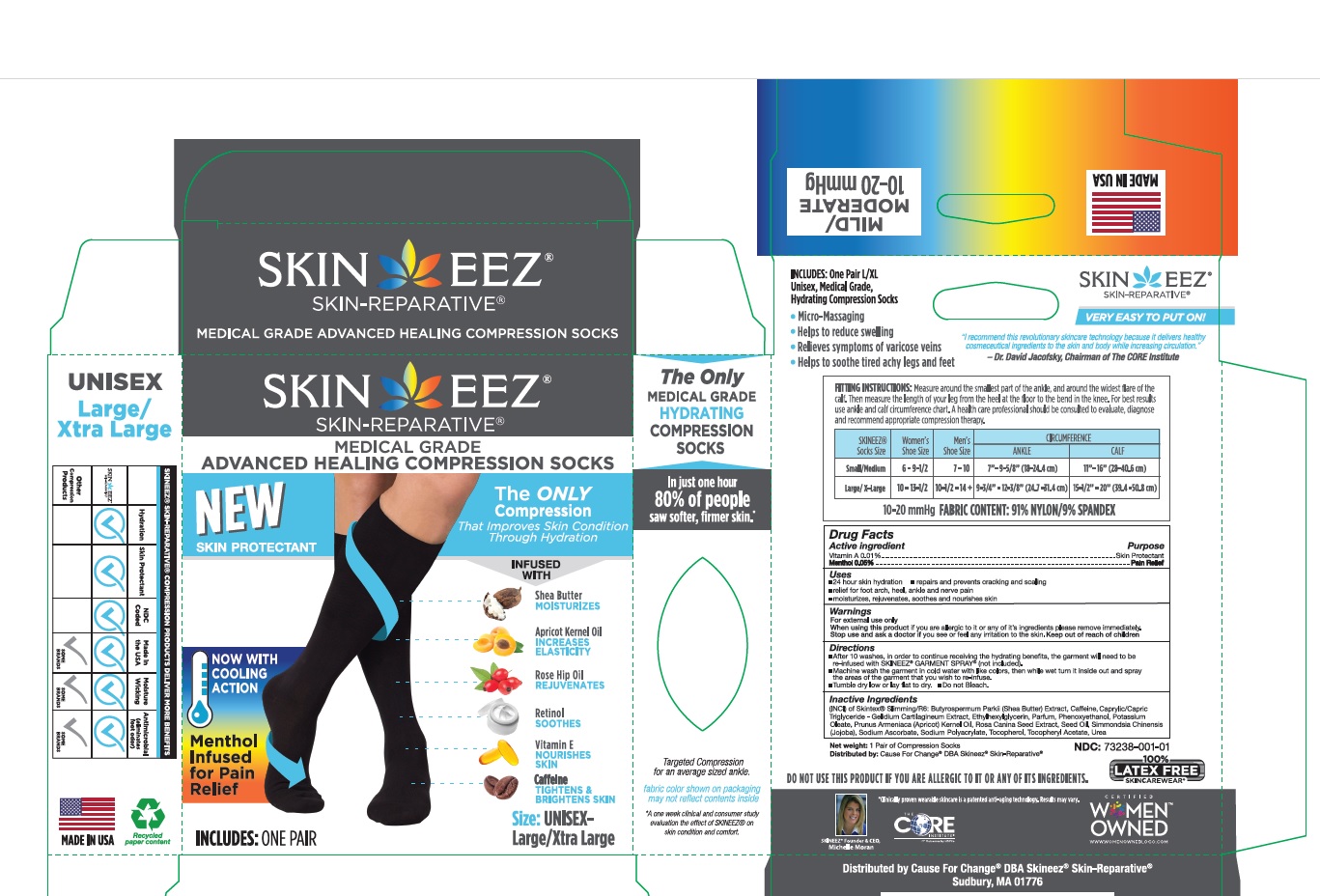 DRUG LABEL: Skineez
NDC: 73238-002 | Form: CLOTH
Manufacturer: CAUSE FOR CHANGE LLC
Category: otc | Type: HUMAN OTC DRUG LABEL
Date: 20251209

ACTIVE INGREDIENTS: MENTHOL 0.05 g/4.66 g; VITAMIN A 0.01 g/4.66 g
INACTIVE INGREDIENTS: SHEA BUTTER; APRICOT KERNEL OIL; PLOCAMIUM CARTILAGINEUM; POTASSIUM OLEATE; JOJOBA OIL; ROSA CANINA SEED; PHENOXYETHANOL; TOCOPHEROL; SODIUM POLYACRYLATE (8000 MW); CAFFEINE; UREA; ETHYLHEXYLGLYCERIN; SODIUM ASCORBATE

Active ingredient Purpose

Vitamin A 0.01% --------------------- Skin protectant

Menthol 0.05% ---------------------- Pain Relief

Uses

- 24 hour skin hydration
- repairs and prevents cracking and scaling
- relief for foot arch, heel, ankle and nerve pain
- moisturizes, rejuvenates, soothes and nourishes skin

Warnings

For external use only

When using this product if you are allergic to it or any of it's ingredients please remove immmediately.

Stop use and ask a doctor ifyou see or feel any irritation to the skin.

Directions

• After 10 washes, in order to continue receiving the hydrating benefits, the garment will need to be re-infused with SKINEEZ® GARMENT SPRAY® (not included).
• Machine wash the garment in cold water with like colors, then while wet turn it inside out and spray the areas of the garment that you wish to re-infuse.
• Tumble dry low or lay flat to dry.
• Do not Bleach.

Inactive ingredients

(INCI) of Skintex® Slimming/R6: Butyrospermum Parkii (Shea Butter) Extract, Caffeine, Caprylic/Capric Triglyceride - Gelidium Cartilagineum Extract, Ethylhexylglycerin, Parfum, Phenoxyethanol, Potassium Oleate, Prunus Armeniaca (Apricot) Kernel Oil, Rosa Canina Seed Extract, Seed Oil, Simmondsia Chinensis (Jojoba), Sodium Ascorbate, Sodium Polyacrylate, Tocopherol, Tocopheryl Acetate, Urea